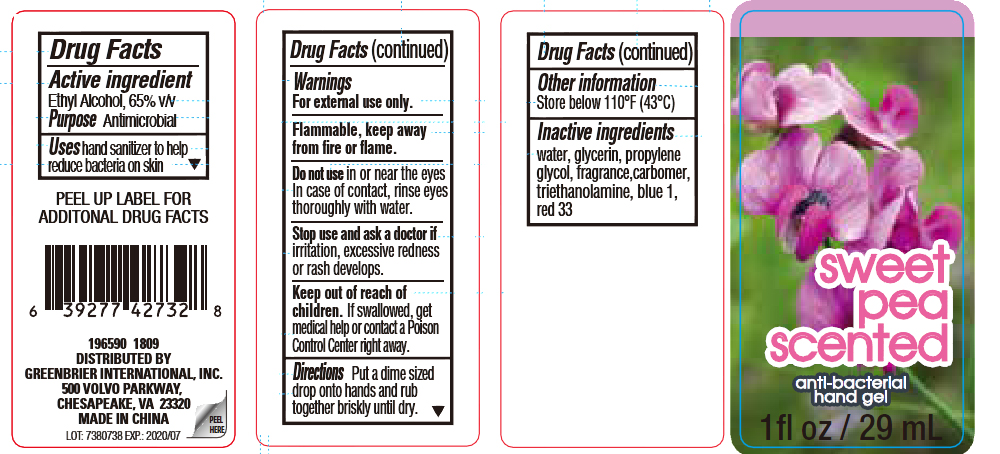 DRUG LABEL: sweet pea scented antimicrobial hand gel
NDC: 43473-824 | Form: LIQUID
Manufacturer: Nantong Health & Beyond Hygienic Products Inc.
Category: otc | Type: HUMAN OTC DRUG LABEL
Date: 20180322

ACTIVE INGREDIENTS: ALCOHOL 65 g/100 mL
INACTIVE INGREDIENTS: WATER; GLYCERIN; PROPYLENE GLYCOL; CARBOMER INTERPOLYMER TYPE A (ALLYL SUCROSE CROSSLINKED); TROLAMINE; FD&C BLUE NO. 1; D&C RED NO. 33

Active ingredient

Ethyl Alcohol, 65% v/v

Purpose Antimicrobial

INDICATIONS AND USAGE

Uses hand sanitizer to help

reduce bacteria on skin

Warnings

For external use only.

Flammable, keep away from

fire or flame.

Do not use in or near the eyes

In case of contact, rinse eyes

thoroughly with water.

Stop use and ask a doctor if

irritation, excessive redness

or rash develops.

Keep out of reach of

children. If swallowed, get

medical help or contact a Poison

Control Center right away.

DOSAGE AND ADMINISTRATION

Directions Put a dime sized

drop onto hands and rub

together briskly until dry.

Other information

Store below 110° F (43° C)

Inactive ingredients

water, glycerin, propylene

glycol, fragrance, carbomer,

triethanolamine, blue 1,

red 33